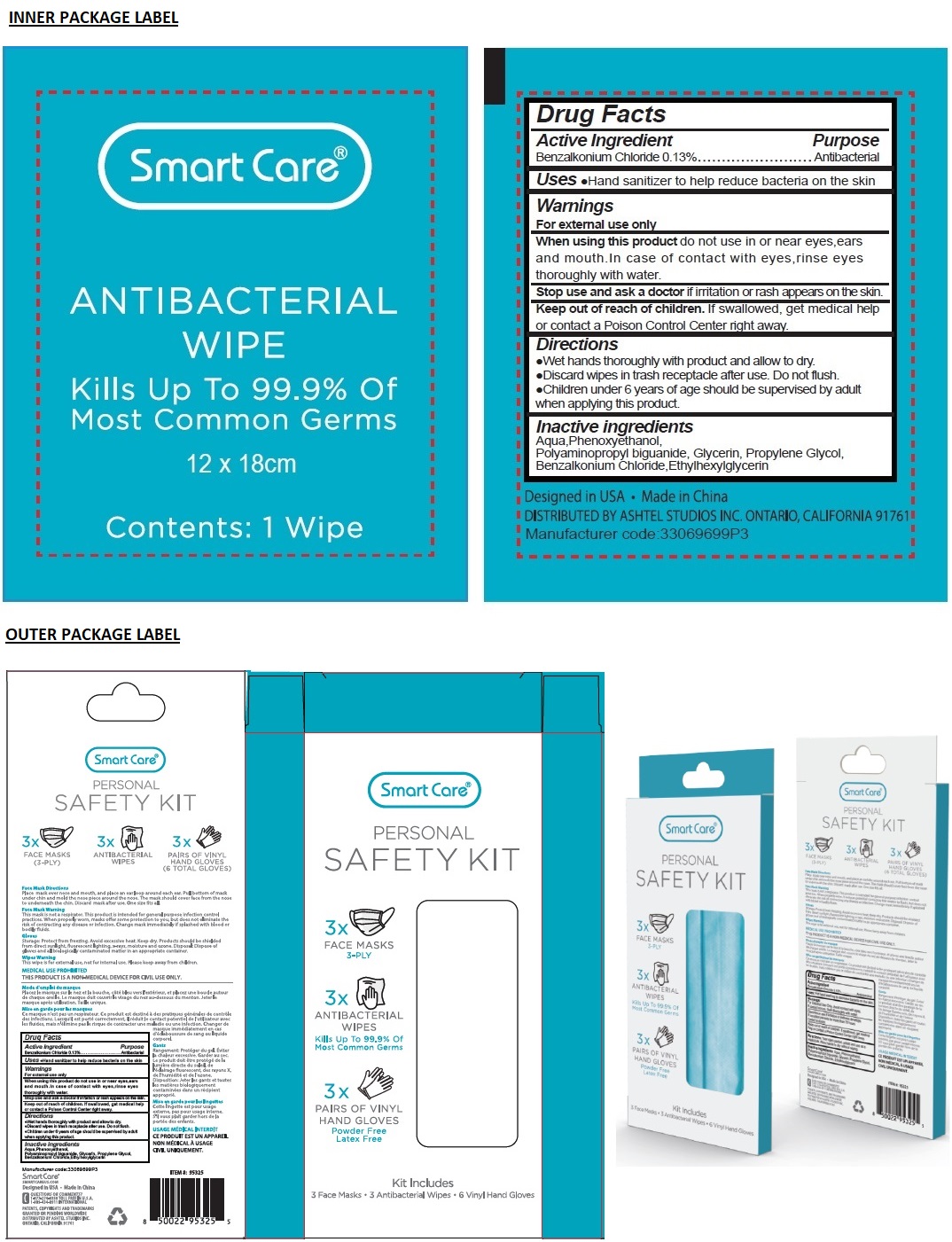 DRUG LABEL: Smart Care Personal Safety Kit
NDC: 70108-072 | Form: CLOTH
Manufacturer: Ashtel Studios, Inc
Category: otc | Type: HUMAN OTC DRUG LABEL
Date: 20210608

ACTIVE INGREDIENTS: BENZALKONIUM CHLORIDE 0.13 g/100 mL
INACTIVE INGREDIENTS: WATER; PHENOXYETHANOL; POLYAMINOPROPYL BIGUANIDE; GLYCERIN; PROPYLENE GLYCOL; ETHYLHEXYLGLYCERIN

Smart Care® PERSONAL SAFETY KIT

Active Ingredient

Benzalkonium Chloride 0.13%

Purpose

Antibacterial

Uses

•Hand sanitizer to help reduce bacteria on the skin

Warnings

For external use only

When using this product do not use in or near eyes, ears and mouth.In case of contact with eyes, rinse eyes thoroughly with water.

Stop use and ask a doctor if irritation or rash appears on the skin.

Keep out of reach of children. If swallowed, get medical help or contact a Poison Control Center right away.

Directions

•Wet hands thoroughly with product and allow to dry.
•Discard wipes in trash receptacle after use. Do not flush.
•Children under 6 years of age should be supervised by adult when applying this product.

Inactive ingredients

Aqua,Phenoxyethanol, Polyaminopropyl biguanide, Glycerin, Propylene Glycol, Benzalkonium Chloride,Ethylhexylglycerin

3x FACE MASKS
3-PLY

3x ANTIBACTERIAL WIPES
Kills Up To 99.9% Of Most Common Germs

3x PAIRS OF VINYL HAND GLOVES
Powder Free
Latex Free

Kit Includes
3 Face Masks • 3 Antibacterial Wipes • 6 Vinyl Hand Gloves

Face Mask Directions
Place mask over nose and mouth, and place an ear loop around each ear. Pull bottom of mask under chin and mold the nose piece around the nose. The mask should cover face from the nose to underneath the chin. Discard mask after use. One size fits all.

Face Mask Warning
This mask is not a respirator. This product is intended for general purpose infection control practices. When properly worn, masks offer some protection to you, but does not eliminate the risk of contracting any disease or infection. Change mask immediately if splashed with blood or bodily fluids.

Gloves
Storage: Protect from freezing. Avoid excessive heat. Keep dry. Products should be shielded from direct sunlight, fluorescent lighting, x-rays, moisture and ozone. Disposal: Dispose of gloves and all biologically contaminated matter in an appropriate container.

Wipes Warning
This wipe is for external use, not for internal use. Please keep away from children.

MEDICAL USE PROHIBITED
THIS PRODUCT IS A NON-MEDICAL DEVICE FOR CIVIL USE ONLY.

Smart Care®
SMARTCAREUS.COM
Designed in USA • Made in China

QUESTIONS OR COMMENTS?
1-877-274-8358 TOLL FREE IN U.S.A.
1-909-434-0911 INTERNATIONAL

PATENTS, COPYRIGHTS, AND TRADEMARKS GRANTED OR PENDING WORLDWIDE
DISTRIBUTED BY ASHTEL STUDIOS INC.
ONTARIO, CALIFORNIA 91761